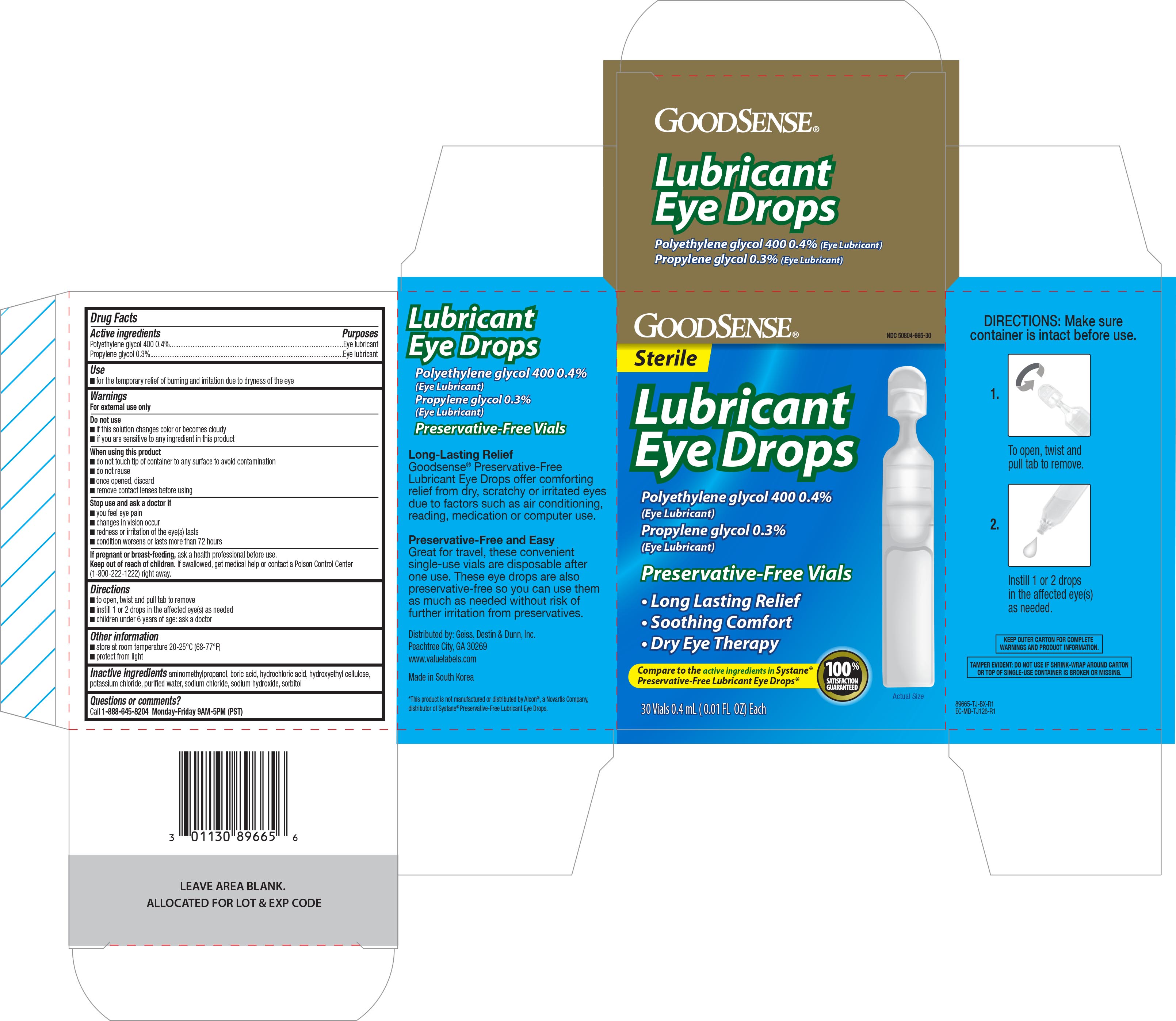 DRUG LABEL: GoodSense Lubricant Eye
NDC: 50804-665 | Form: SOLUTION/ DROPS
Manufacturer: Geiss, Destin & Dunn, Inc
Category: otc | Type: HUMAN OTC DRUG LABEL
Date: 20180420

ACTIVE INGREDIENTS: POLYETHYLENE GLYCOL 400 4 mg/1 mL; PROPYLENE GLYCOL 3 mg/1 mL
INACTIVE INGREDIENTS: SODIUM HYDROXIDE; SORBITOL; SODIUM CHLORIDE; AMINOMETHYLPROPANOL; HYDROCHLORIC ACID; BORIC ACID; POTASSIUM CHLORIDE; WATER

GoodSense Lubricant Eye Drops 30 ct. NBE Systane 5474 (2018)

Active ingredients Purposes

Polyethylene glycol 400 0.4%........................................Eye lubricant

Propylene glycol 0.3%...................................................Eye lubricant

Use

- for the temporary relief of burning and irritation due to dryness of the eye

Warnings

For external use only

Do not use

- if the solution changes color or becomes cloudy
- if you are sensitive to any ingredient in this product

When using this product

- do not touch tip of container to any surface to avoid contamination
- do not reuse
- once opened, discard
- remove contact lenses before using

Stop use and ask a doctor if

- you feel eye pain
- changes in vision occur
- redness or irritation of the eye(s) lasts
- condition worsens or lasts more than 72 hours

PREGNANCY OR BREAST FEEDING

If pregnant or breast-feeding, ask a health professional before use.

Keep out of reach of children. If swallowed, get medical help or contact a Poison Control Center (1-800-222-1222) right away.

Directions

- to open, twist and pull tab to remove
- instill 1 or 2 drops in the affected eye(s) as needed
- children under 6 years of age: ask a doctor

Other information

- store at room temperature 20-25°C (68-77°F)
- protect from light

Inactive ingredients

aminomethylpropanol, boric acid, hydrochlorid acid, hydroxyethyl cellulose, potassium chloride, purified water, sodium chloride, sodium hydroxide, sorbitol

DOSAGE AND ADMINISTRATION

Distributed by:

Geiss, Destin & Dunn, Inc.

Peachtree City, GA 30269

www.valuelabels.com

Made in South Korea